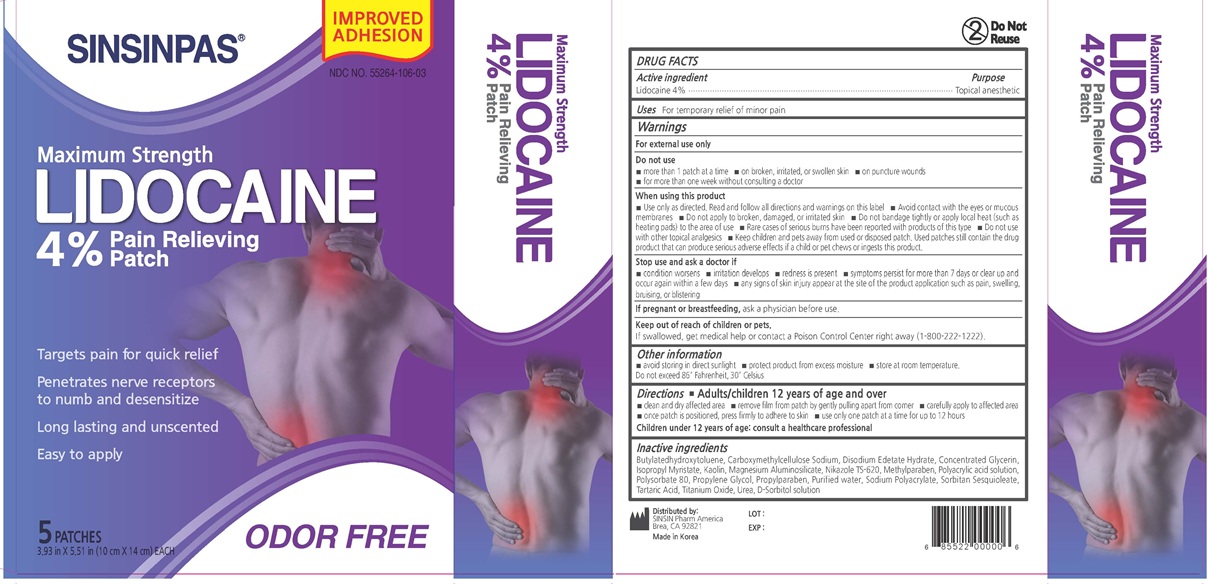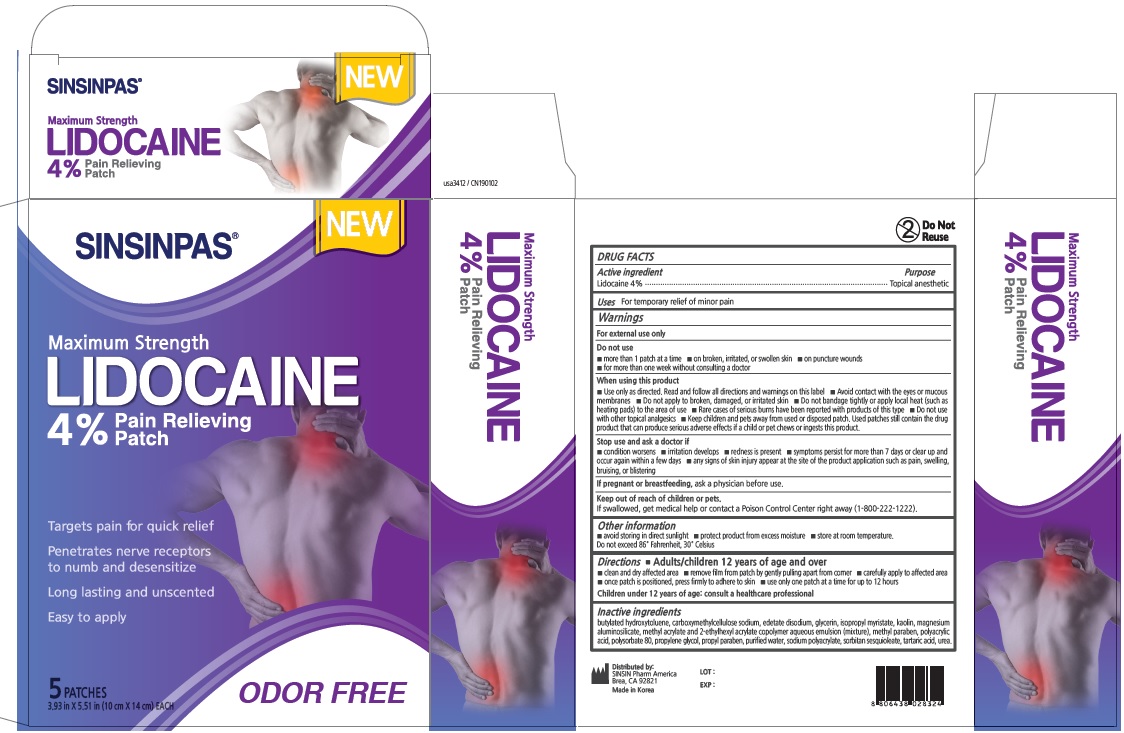 DRUG LABEL: SINSINPAS LIDOCAINE PAIN RELIEVING
NDC: 55264-106 | Form: PATCH
Manufacturer: Sinsin Pharmaceutical Co., Ltd.
Category: otc | Type: HUMAN OTC DRUG LABEL
Date: 20251007

ACTIVE INGREDIENTS: LIDOCAINE 560 mg/14 g
INACTIVE INGREDIENTS: ISOPROPYL MYRISTATE 280 mg/14 g; BUTYLATED HYDROXYTOLUENE; GLYCERIN 3500 mg/14 g

SINSINPAS LIDOCAINE PAIN RELIEVING PATCH

Active Ingredients

Lidocaine 4%

Purpose

Topical Anesthetic

Keep out of reach of children or pets

If swallowed, get medical help or contact a Poison Control Center (1-800-222-1222)

Uses

For the temporarily relief of minor pain

Warnings

For external use only

Do not use

- more than 1 patch at a time
- on broken, irritated, or swollen skin
- on puncture wounds
- for more than one week without consulting a doctor

When using this product

- use only as directed. Read and follow all direction and warning on this label
- Avoid contact with the eyes or mucous membranes
- Do not apply to broken, damaged, or irritated skin
- Do not bandage tightly or apply local heat (such as heating pads) to the area of use
- Rare cases of serious burns have been reported with products of this type
- Do not use with other topical analgesics
- Keep children and pets away from used or disposed patch.
- Used patches still contain the drug product that can produce serious adverse effects if a child or pet chews or ingests this product.

Directions

Adults and children 12 years of age and over:

- clean and dry affected area
- remove film from patch by gently pulling apart from corner
- carefully apply to afftcted area
- once patch is positioned, press firmly to adhere to skin
- use only one patch at a time for up the 12 hours

Children under 12 years of age: consult a professional

Inactive Ingredients

butylated hydroxytoluene
carboxymethylcellulose sodium
glycerin
edetate disodium
isopropyl myristate
kaolin
magnesium aluminosilicate
methyl acrylate and 2-ethylhexyl acrylate copolymer aqueous emulsion (mixture)
methyl paraben
polyacrylic acid
polysorbate 80
propylene glycol
propyl paraben
purified water
sodium polyacrylate
sorbitan sesquioleate
tartaric acid
urea